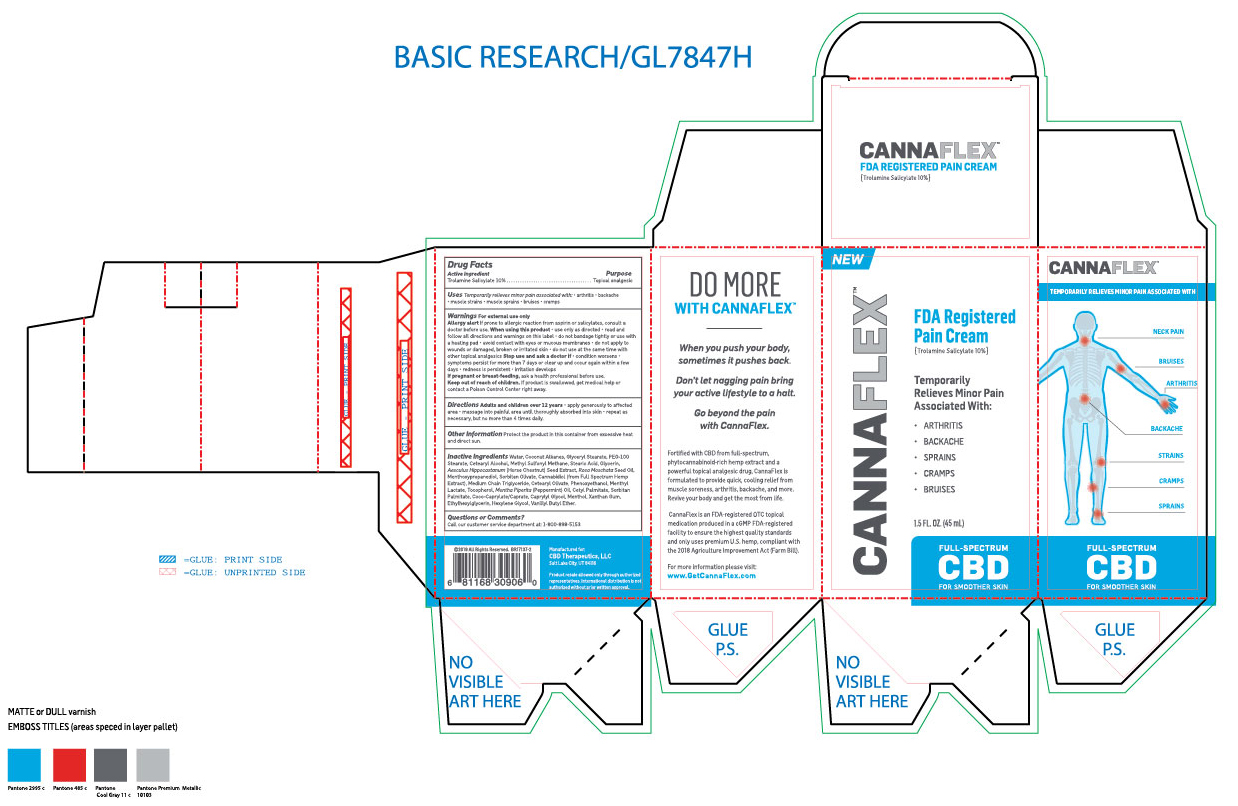 DRUG LABEL: Cannaflex
NDC: 62742-4177 | Form: CREAM
Manufacturer: ALLURE LABS INC.
Category: otc | Type: HUMAN OTC DRUG LABEL
Date: 20191016

ACTIVE INGREDIENTS: TROLAMINE SALICYLATE 100 mg/1 mL
INACTIVE INGREDIENTS: WATER; COCONUT ALKANES; GLYCERYL MONOSTEARATE; PEG-100 STEARATE; CETOSTEARYL ALCOHOL; DIMETHYL SULFONE; STEARIC ACID; GLYCERIN; HORSE CHESTNUT; ROSA MOSCHATA SEED OIL; 3-((L-MENTHYL)OXY)PROPANE-1,2-DIOL; SORBITAN OLIVATE; CANNABIDIOL; MEDIUM-CHAIN TRIGLYCERIDES; CETEARYL OLIVATE; PHENOXYETHANOL; MENTHYL LACTATE, (-)-; TOCOPHEROL; PEPPERMINT OIL; CETYL PALMITATE; SORBITAN MONOPALMITATE; COCO-CAPRYLATE/CAPRATE; CAPRYLYL GLYCOL; MENTHOL; XANTHAN GUM; ETHYLHEXYLGLYCERIN; HEXYLENE GLYCOL; VANILLYL BUTYL ETHER

DRUG FACTS

Active Ingredients:

Trolamine Salicylate - 10%

Purpose:

Topical Analgesic

INDICATIONS AND USAGE

Uses: Temporarily relieves minor pain associated with arthritis, backache, muscle strains, muscle sprains, bruises, cramps.

WARNINGS

Warning: For external use only.

Allergy alert if prone to allergic reaction from aspirin or salicylates, consult a Doctor before use.

When using this product: Use only as directed. Read and follow all directions and warnings on this label. Do not bandage tightly or use with a heated pad. Avoid contact with eyes or mucous membranes. Do not apply to wounds or damaged, broken or irritated skin. Do not use at the same time with other topical analgesics.

Stop use and ask a doctor if condition worsens. Symptoms persist for more than 7 days or clear up and occur again within a few days. Redness is persistent. Irritation develops.

PREGNANCY OR BREAST FEEDING

If pregnant or breast-feeding, ask a health professional before use.

Keep out of reach of children. If product swallowed, get medical help or contact a Poison Control Center right away.

INACTIVE INGREDIENT

Inactive ingredients: Water, Coconut Alkanes, Glyceryl Stearate, PEG-100 Stearate, Cetearyl Alcohol, Methyl Sulfonyl Methane, Stearic Acid, Glycerin, Aesculus Hippocastannum (Horse Chestnut) Seed Extract, Rosa Moschata Seed Oil, Menthoxypropanediol, Sorbitan Olivate, Cannabidiol (From full spectrum hemp extract), Medium Chain Triglyceride, Cetearyl Olivate, Phenoxyethanol, Menthyl Lactate, Tocopherol, Mentha Piperita (Pepperment) Oil, Cetyl Palmitate, Sorbitan Palmitate, Coco-Caprylate/Caprate, Caprylyl Glycol, Menthol, Xanthan Gum, Ethylhexylglycerin, Hexylene Glycol, Vanillyl Butyl Ether.

DOSAGE AND ADMINISTRATION

Adults and Children over 12 years: Apply generously to affected area. Massage into painful area until thoroughly asborbed into skin. Repeat as necessary, But no more than 4 times daily.

Questions or Comments?

Call our customer service department at: 1-800-898-5153

PACKAGE LABEL

Manufactured for:

CBD Therapeutics, LLC

Salt Lake City, UT 84116